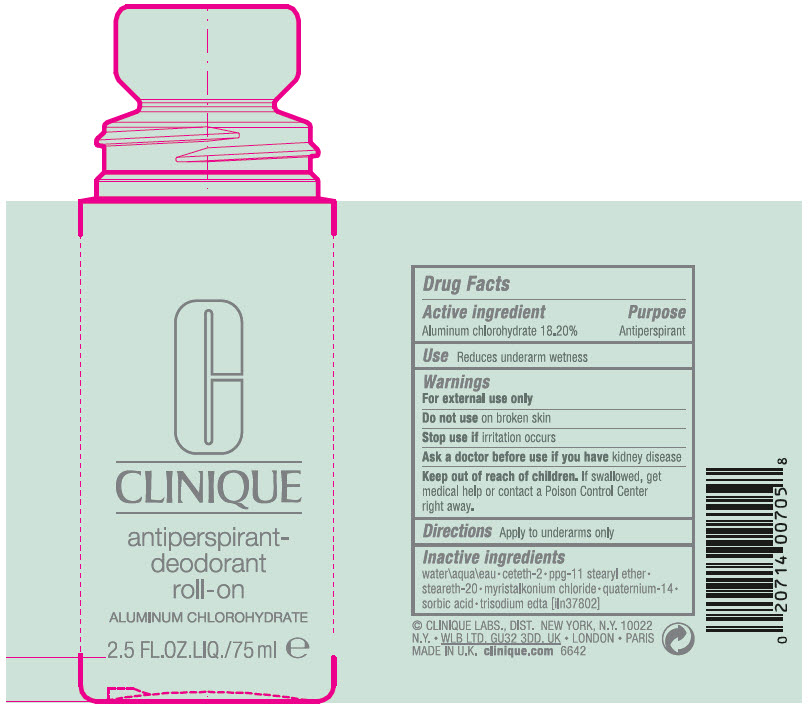 DRUG LABEL: ANTIPERSPIRANT-DEODORANT ROLL-ON
NDC: 49527-076 | Form: LIQUID
Manufacturer: CLINIQUE LABORATORIES LLC
Category: otc | Type: HUMAN OTC DRUG LABEL
Date: 20231019

ACTIVE INGREDIENTS: ALUMINUM CHLOROHYDRATE 182 mg/1 mL
INACTIVE INGREDIENTS: WATER; CETETH-2; POLYPROPYLENE GLYCOL 11 STEARYL ETHER; STEARETH-20; MYRISTALKONIUM CHLORIDE; QUATERNIUM-14; SORBIC ACID; EDETATE TRISODIUM

ANTIPERSPIRANT-DEODORANT ROLL-ON

Drug Facts

Active ingredient

Aluminum chlorohydrate 18.20%

Purpose

Antiperspirant

Use

Reduces underarm wetness

Warnings

For external use only

Do not use on broken skin

Stop use if irritation occurs

Ask a doctor before use if you have kidney disease

Keep out of reach of children. If swallowed, get medical help or contact a Poison Control Center right away.

Directions

Apply to underarms only

Inactive ingredients

water\aqua\eau • ceteth-2 • ppg-11 stearyl ether • steareth-20 • myristalkonium chloride • quaternium-14 • sorbic acid • trisodium edta [iln37802]

PRINCIPAL DISPLAY PANEL - 75 ml Bottle Label

C
CLINIQUE

antiperspirant-
deodorant
roll-on

ALUMINUM CHLOROHYDRATE

2.5 FL.OZ.LIQ./75 ml e